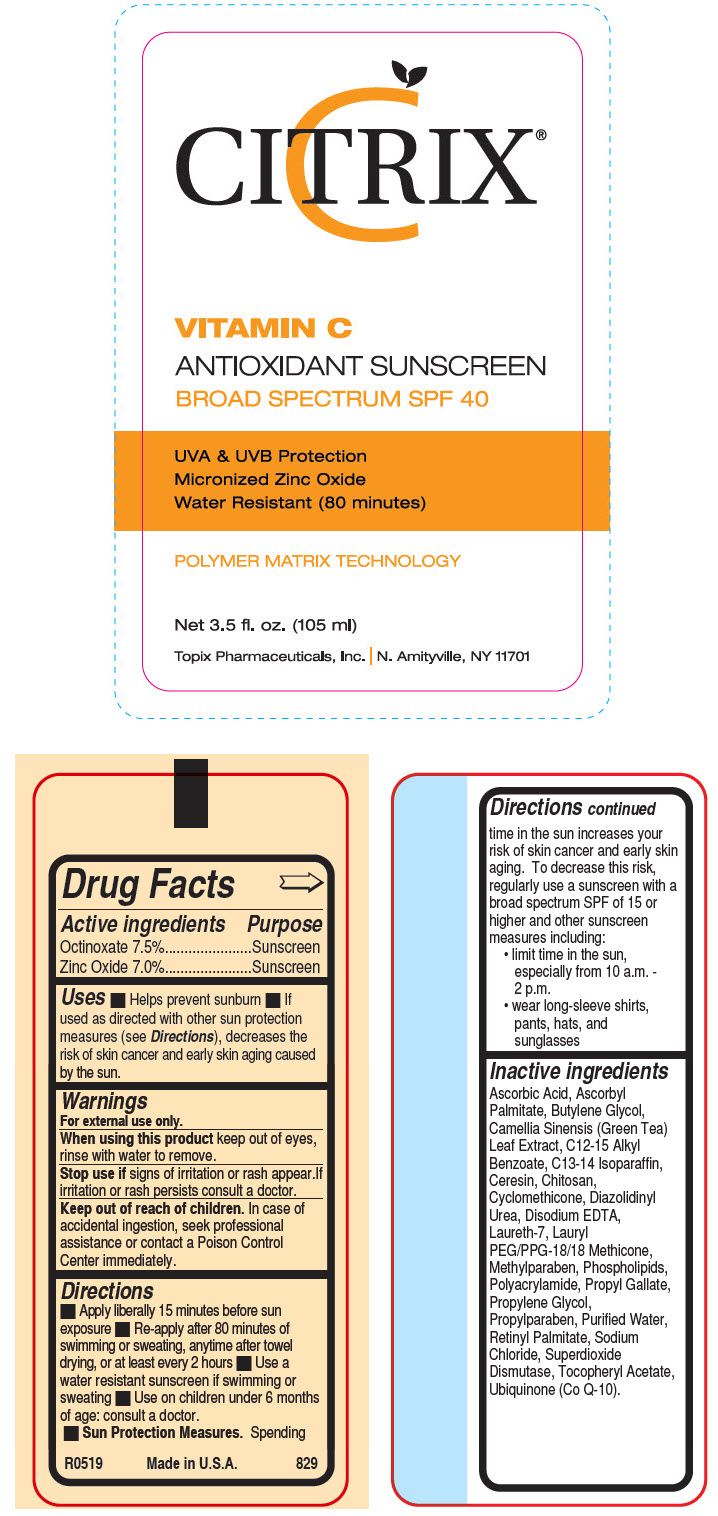 DRUG LABEL: Antioxidant Sunscreen SPF 40
NDC: 51326-829 | Form: LOTION
Manufacturer: Topiderm, Inc.
Category: otc | Type: HUMAN OTC DRUG LABEL
Date: 20191113

ACTIVE INGREDIENTS: OCTINOXATE 75 mg/1 mL; ZINC OXIDE 70 mg/1 mL
INACTIVE INGREDIENTS: ASCORBIC ACID; ASCORBYL PALMITATE; BUTYLENE GLYCOL; GREEN TEA LEAF; ALKYL (C12-15) BENZOATE; C13-14 ISOPARAFFIN; CERESIN; CHITOSAN LOW MOLECULAR WEIGHT (20-200 MPA.S); CYCLOMETHICONE; DIAZOLIDINYL UREA; EDETATE DISODIUM ANHYDROUS; LAURETH-7; LAURYL PEG/PPG-18/18 METHICONE; METHYLPARABEN; LECITHIN, SOYBEAN; POLYACRYLAMIDE (1500 MW); PROPYL GALLATE; PROPYLENE GLYCOL; PROPYLPARABEN; WATER; VITAMIN A PALMITATE; SODIUM CHLORIDE; SUPEROXIDE DISMUTASE (SACCHAROMYCES CEREVISIAE); .ALPHA.-TOCOPHEROL ACETATE; UBIDECARENONE

Vit C Antioxidant Sunscreen SPF 40

Drug Facts

ACTIVE INGREDIENT

Active ingredients | Purpose
Octinoxate 7.5% | Sunscreen
Zinc Oxide 7.0% | Sunscreen

Uses

- Helps prevent sunburn
- If used as directed with other sun protection measures (see Directions), decreases the risk of skin cancer and early skin aging caused by the sun.

Warnings

For external use only.

When using this product keep out of eyes, rinse with water to remove.

Stop use if signs of irritation or rash appear.If irritation or rash persists consult a doctor.

Keep out of reach of children. In case of accidental ingestion, seek professional assistance or contact a Poison Control Center immediately.

Directions

- Apply liberally 15 minutes before sun exposure
- Re-apply after 80 minutes of swimming or sweating, anytime after towel drying, or at least every 2 hours
- Use a water resistant sunscreen if swimming or sweating
- Use on children under 6 months of age: consult a doctor.
- Sun Protection Measures. Spending time in the sun increases your risk of skin cancer and early skin aging. To decrease this risk, regularly use a sunscreen with a broad spectrum SPF of 15 or higher and other sunscreen measures including:
  - limit time in the sun, especially from 10 a.m. - 2 p.m.
  - wear long-sleeve shirts, pants, hats, and sunglasses

Inactive ingredients

Ascorbic Acid, Ascorbyl Palmitate, Butylene Glycol, Camellia Sinensis (Green Tea) Leaf Extract, C12-15 Alkyl Benzoate, C13-14 Isoparaffin, Ceresin, Chitosan, Cyclomethicone, Diazolidinyl Urea, Disodium EDTA, Laureth-7, Lauryl PEG/PPG-18/18 Methicone, Methylparaben, Phospholipids, Polyacrylamide, Propyl Gallate, Propylene Glycol, Propylparaben, Purified Water, Retinyl Palmitate, Sodium Chloride, Superdioxide Dismutase, Tocopheryl Acetate, Ubiquinone (Co Q-10).

PRINCIPAL DISPLAY PANEL - 105 ml Bottle Label

CITRIX®

VITAMIN C
ANTIOXIDANT SUNSCREEN
BROAD SPECTRUM SPF 40

UVA & UVB Protection
Micronized Zinc Oxide
Water Resistant (80 minutes)

POLYMER MATRIX TECHNOLOGY

Net 3.5 fl. oz. (105 ml)
Topix Pharmaceuticals, Inc. | N. Amityville, NY 11701